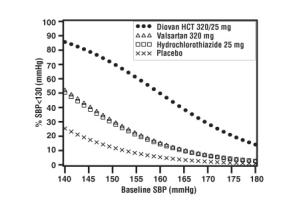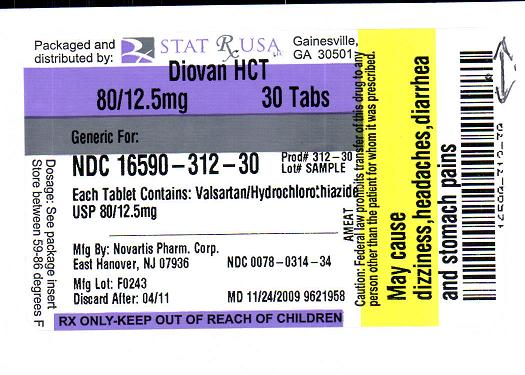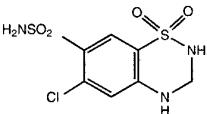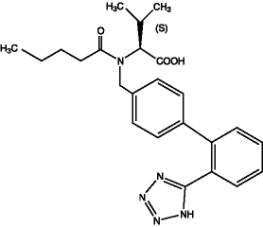 DRUG LABEL: DIOVAN HCT
NDC: 16590-312 | Form: TABLET, FILM COATED
Manufacturer: STAT RX USA LLC
Category: prescription | Type: HUMAN PRESCRIPTION DRUG LABEL
Date: 20091228

ACTIVE INGREDIENTS: HYDROCHLOROTHIAZIDE 12.5 mg/1 1; VALSARTAN 80 mg/1 1

11 DESCRIPTION

Diovan HCT (valsartan and hydrochlorothiazide, USP) is a combination of valsartan, an orally active, specific angiotensin II receptor blocker (ARB) acting on the AT1 receptor subtype, and hydrochlorothiazide, a diuretic.

Valsartan, a nonpeptide molecule, is chemically described as N-(1-oxopentyl)-N-[[2′-(1H-tetrazol-5-yl)[1,1′-biphenyl]-4-yl]methyl]-L-Valine. Its empirical formula is C24H29N5O3, its molecular weight is 435.5, and its structural formula is

Valsartan is a white to practically white fine powder. It is soluble in ethanol and methanol and slightly soluble in water.

Hydrochlorothiazide USP is a white, or practically white, practically odorless, crystalline powder. It is slightly soluble in water; freely soluble in sodium hydroxide solution, in n-butylamine, and in dimethylformamide; sparingly soluble in methanol; and insoluble in ether, in chloroform, and in dilute mineral acids. Hydrochlorothiazide is chemically described as 6-chloro-3,4-dihydro-2H-1,2,4-benzothiadiazine-7-sulfonamide 1,1-dioxide.

Hydrochlorothiazide is a thiazide diuretic. Its empirical formula is C7H8ClN3O4S2, its molecular weight is 297.73, and its structural formula is

Diovan HCT tablets are formulated for oral administration to contain valsartan and hydrochlorothiazide, USP 80/12.5 mg, 160/12.5 mg, 160/25 mg, 320/12.5 mg and 320/25 mg. The inactive ingredients of the tablets are colloidal silicon dioxide, crospovidone, hydroxypropyl methylcellulose, iron oxides, magnesium stearate, microcrystalline cellulose, polyethylene glycol, talc, and titanium dioxide.

INDICATIONS AND USAGE

Diovan HCT (valsartan and hydrochlorothiazide, USP) is indicated for the treatment of hypertension.

Diovan HCT may be used in patients whose blood pressure is not adequately controlled on monotherapy.

Diovan HCT may be used as initial therapy in patients who are likely to need multiple drugs to achieve blood pressure goals.

The choice of Diovan HCT as initial therapy for hypertension should be based on an assessment of potential benefits and risks.

Patients with stage 2 hypertension are at a relatively high risk for cardiovascular events (such as strokes, heart attacks, and heart failure), kidney failure, and vision problems, so prompt treatment is clinically relevant. The decision to use a combination as initial therapy should be individualized and should be shaped by considerations such as baseline blood pressure, the target goal and the incremental likelihood of achieving goal with a combination compared to monotherapy. Individual blood pressure goals may vary based upon the patient’s risk.

Data from the high dose multifactorial trial [See Clinical Studies (14.1)] provides estimates of the probability of reaching a target blood pressure with Diovan HCT compared to valsartan or hydrochlorothiazide monotherapy. The figures below provide estimates of the likelihood of achieving systolic or diastolic blood pressure control with Diovan HCT 320/25 mg, based upon baseline systolic or diastolic blood pressure. The curve of each treatment group was estimated by logistic regression modeling. The estimated likelihood at the right tail of each curve is less reliable due to small numbers of subjects with high baseline blood pressures.
For example, a patient with a baseline blood pressure of 160/100 mmHg has about a 41% likelihood of achieving a goal of less than 140 mmHg (systolic) and 60% likelihood of achieving less than 90 mmHg (diastolic) on valsartan alone and the likelihood of achieving these goals on HCTZ alone is about 50% (systolic) or 57% (diastolic). The likelihood of achieving these goals on Diovan HCT rises to about 84% (systolic) or 80% (diastolic). The likelihood of achieving these goals on placebo is about 23% (systolic) or 36% (diastolic).

CONTRAINDICATIONS

Diovan HCT (valsartan and hydrochlorothiazide, USP) is contraindicated in patients who are hypersensitive to any component of this product.

Because of the hydrochlorothiazide component, this product is contraindicated in patients with anuria or hypersensitivity to other sulfonamide-derived drugs.

ADVERSE REACTIONS 6.1 Clinical Trials Experience

Because clinical studies are conducted under widely varying conditions, adverse reactions rates observed in the clinical studies of a drug cannot be directly compared to rates in the clinical studies of another drug and may not reflect the rates observed in practice. The adverse reaction information from clinical trials does, however, provide a basis for identifying the adverse events that appear to be related to drug use and for approximating rates.

Hypertension

Diovan HCT (valsartan and hydrochlorothiazide, USP) has been evaluated for safety in more than 5,700 patients, including over 990 treated for over 6 months, and over 370 for over 1 year. Adverse experiences have generally been mild and transient in nature and have only infrequently required discontinuation of therapy. The overall incidence of adverse reactions with Diovan HCT was comparable to placebo.

The overall frequency of adverse reactions was neither dose-related nor related to gender, age, or race. In controlled clinical trials, discontinuation of therapy due to side effects was required in 2.3% of valsartan-hydrochlorothiazide patients and 3.1% of placebo patients. The most common reasons for discontinuation of therapy with Diovan HCT were headache and dizziness.

The only adverse reaction that occurred in controlled clinical trials in at least 2% of patients treated with Diovan HCT and at a higher incidence in valsartan-hydrochlorothiazide (n=4372) than placebo (n=262) patients was nasopharyngitis (2.4% vs. 1.9%).

Dose-related orthostatic effects were seen in fewer than 1% of patients. In individual trials, a dose-related increase in the incidence of dizziness was observed in patients treated with Diovan HCT.

Other adverse reactions that have been reported with valsartan-hydrochlorothiazide (>0.2% of valsartan-hydrochlorothiazide patients in controlled clinical trials) without regard to causality, are listed below:

Cardiovascular: Palpitations and tachycardia

Ear and Labyrinth: Tinnitus and vertigo

Gastrointestinal: Dyspepsia, diarrhea, flatulence, dry mouth, nausea, abdominal pain, abdominal pain upper, and vomiting

General and Administration Site Conditions: Asthenia, chest pain, fatigue, peripheral edema and pyrexia

Infections and Infestations: Bronchitis, bronchitis acute, influenza, gastroenteritis, sinusitis, upper respiratory tract infection and urinary tract infection

Investigations: Blood urea increased

Musculoskeletal: Arthralgia, back pain, muscle cramps, myalgia, and pain in extremity

Nervous System: Dizziness postural, paresthesia, and somnolence

Psychiatric: Anxiety and insomnia

Renal and Urinary: Pollakiuria

Reproductive System: Erectile dysfunction

Respiratory, Thoracic and Mediastinal: Dyspnea, cough, nasal congestion, pharyngolaryngeal pain and sinus congestion

Skin and Subcutaneous Tissue: Hyperhidrosis and rash

Vascular: Hypotension

Other reported reactions seen less frequently in clinical trials included abnormal vision, anaphylaxis, bronchospasm, constipation, depression, dehydration, decreased libido, dysuria, epistaxis, flushing, gout, increased appetite, muscle weakness, pharyngitis, pruritus, sunburn, syncope, and viral infection

Valsartan: In trials in which valsartan was compared to an ACE inhibitor with or without placebo, the incidence of dry cough was significantly greater in the ACE inhibitor group (7.9%) than in the groups who received valsartan (2.6%) or placebo (1.5%). In a 129-patient trial limited to patients who had had dry cough when they had previously received ACE inhibitors, the incidences of cough in patients who received valsartan, hydrochlorothiazide, or lisinopril were 20%, 19%, 69% respectively (p less than 0.001).

Other reported reactions seen less frequently in clinical trials included chest pain, syncope, anorexia, vomiting, and angioedema.

Hydrochlorothiazide: Other adverse reactions that have been reported with hydrochlorothiazide, without regard to causality, are listed below:

Body As A Whole: weakness

Digestive: pancreatitis, jaundice (intrahepatic cholestatic jaundice), sialadenitis, cramping, gastric irritation;

Hematologic: aplastic anemia, agranulocytosis, leukopenia, hemolytic anemia, thrombocytopenia;

Hypersensitivity: purpura, photosensitivity, urticaria, necrotizing angiitis (vasculitis and cutaneous vasculitis), fever, respiratory distress including pneumonitis and pulmonary edema, anaphylactic reactions;

Metabolic: hyperglycemia, glycosuria, hyperuricemia;

Musculoskeletal: muscle spasm;

Nervous System/Psychiatric: restlessness;

Renal: renal failure, renal dysfunction, interstitial nephritis;

Skin: erythema multiforme including Stevens-Johnson syndrome, exfoliative dermatitis including toxic epidermal necrolysis;

Special Senses: transient blurred vision, xanthopsia.

Initial Therapy - Hypertension

In a clinical study in patients with severe hypertension (diastolic blood pressure greater than or equal to 110 mmHg and systolic blood pressure greater than or equal to 140 mmHg), the overall pattern of adverse reactions reported through six weeks of follow-up was similar in patients treated with Diovan HCT as initial therapy and in patients treated with valsartan as initial therapy. Comparing the groups treated with Diovan HCT (force-titrated to 320/25 mg) and valsartan (force-titrated to 320 mg), dizziness was observed in 6% and 2% of patients, respectively. Hypotension was observed in 1% of those patients receiving Diovan HCT and 0% of patients receiving valsartan. There were no reported cases of syncope in either treatment group. Laboratory changes with Diovan HCT as initial therapy in patients with severe hypertension were similar to those reported with Diovan HCT in patients with less severe hypertension [See Clinical Studies (14.2) and Drug Interactions (7.3)].

6.2 Postmarketing Experience

The following additional adverse reactions have been reported in valsartan or valsartan/hydrochlorothiazide postmarketing experience:

Hypersensitivity: There are rare reports of angioedema;

Digestive: Elevated liver enzymes and very rare reports of hepatitis;

Renal: Impaired renal function;

Clinical Laboratory Tests: Hyperkalemia;

Dermatologic: Alopecia;

Vascular: Vasculitis;

Nervous System: Syncope.

Rare cases of rhabdomyolysis have been reported in patients receiving angiotensin II receptor blockers.

Because these reactions are reported voluntarily from a population of uncertain size, it is not always possible to reliably estimate their frequency or establish a causal relationship to drug exposure

10 OVERDOSAGE

Valsartan – Hydrochlorothiazide: Limited data are available related to overdosage in humans. The most likely manifestations of overdosage would be hypotension and tachycardia; bradycardia could occur from parasympathetic (vagal) stimulation. Depressed level of consciousness, circulatory collapse and shock have been reported. If symptomatic hypotension should occur, supportive treatment should be instituted.

Valsartan is not removed from the plasma by dialysis.

The degree to which hydrochlorothiazide is removed by hemodialysis has not been established. The most common signs and symptoms observed in patients are those caused by electrolyte depletion (hypokalemia, hypochloremia, hyponatremia) and dehydration resulting from excessive diuresis. If digitalis has also been administered, hypokalemia may accentuate cardiac arrhythmias.

In rats and marmosets, single oral doses of valsartan up to 1524 and 762 mg/kg in combination with hydrochlorothiazide at doses up to 476 and 238 mg/kg, respectively, were very well tolerated without any treatment-related effects. These no adverse effect doses in rats and marmosets, respectively, represent 46.5 and 23 times the maximum recommended human dose (MRHD) of valsartan and 188 and 113 times the MRHD of hydrochlorothiazide on a mg/m^2 basis. (Calculations assume an oral dose of 320 mg/day valsartan in combination with 25 mg/day hydrochlorothiazide and a 60-kg patient.)

Valsartan: Valsartan was without grossly observable adverse effects at single oral doses up to 2000 mg/kg in rats and up to 1000 mg/kg in marmosets, except for salivation and diarrhea in the rat and vomiting in the marmoset at the highest dose (60 and 31 times, respectively, the maximum recommended human dose on a mg/m^2 basis). (Calculations assume an oral dose of 320 mg/day and a 60-kg patient.)

Hydrochlorothiazide: The oral LD50 of hydrochlorothiazide is greater than 10 g/kg in both mice and rats, which represents 2027 and 4054 times, respectively, the maximum recommended human dose on a mg/m^2 basis. (Calculations assume an oral dose of 25 mg/day and a 60-kg patient.)

12 CLINICAL PHARMACOLOGY 12.1 Mechanism of Action

Angiotensin II is formed from angiotensin I in a reaction catalyzed by angiotensin-converting enzyme (ACE, kininase II). Angiotensin II is the principal pressor agent of the renin-angiotensin system, with effects that include vasoconstriction, stimulation of synthesis and release of aldosterone, cardiac stimulation, and renal reabsorption of sodium. Valsartan blocks the vasoconstrictor and aldosterone-secreting effects of angiotensin II by selectively blocking the binding of angiotensin II to the AT1 receptor in many tissues, such as vascular smooth muscle and the adrenal gland. Its action is therefore independent of the pathways for angiotensin II synthesis.

There is also an AT2 receptor found in many tissues, but AT2 is not known to be associated with cardiovascular homeostasis. Valsartan has much greater affinity (about 20,000-fold) for the AT1 receptor than for the AT2 receptor. The primary metabolite of valsartan is essentially inactive with an affinity for the AT1 receptor about one 200th that of valsartan itself.

Blockade of the renin-angiotensin system with ACE inhibitors, which inhibit the biosynthesis of angiotensin II from angiotensin I, is widely used in the treatment of hypertension. ACE inhibitors also inhibit the degradation of bradykinin, a reaction also catalyzed by ACE. Because valsartan does not inhibit ACE (kininase II) it does not affect the response to bradykinin. Whether this difference has clinical relevance is not yet known. Valsartan does not bind to or block other hormone receptors or ion channels known to be important in cardiovascular regulation.

Blockade of the angiotensin II receptor inhibits the negative regulatory feedback of angiotensin II on renin secretion, but the resulting increased plasma renin activity and angiotensin II circulating levels do not overcome the effect of valsartan on blood pressure.

Hydrochlorothiazide is a thiazide diuretic. Thiazides affect the renal tubular mechanisms of electrolyte reabsorption, directly increasing excretion of sodium and chloride in approximately equivalent amounts. Indirectly, the diuretic action of hydrochlorothiazide reduces plasma volume, with consequent increases in plasma renin activity, increases in aldosterone secretion, increases in urinary potassium loss, and decreases in serum potassium. The renin-aldosterone link is mediated by angiotensin II, so coadministration of an angiotensin II receptor antagonist tends to reverse the potassium loss associated with these diuretics.

The mechanism of the antihypertensive effect of thiazides is unknown.

12.2 Pharmacodynamics

Valsartan: Valsartan inhibits the pressor effect of angiotensin II infusions. An oral dose of 80 mg inhibits the pressor effect by about 80% at peak with approximately 30% inhibition persisting for 24 hours. No information on the effect of larger doses is available.

Removal of the negative feedback of angiotensin II causes a 2- to 3-fold rise in plasma renin and consequent rise in angiotensin II plasma concentration in hypertensive patients. Minimal decreases in plasma aldosterone were observed after administration of valsartan; very little effect on serum potassium was observed.

In multiple-dose studies in hypertensive patients with stable renal insufficiency and patients with renovascular hypertension, valsartan had no clinically significant effects on glomerular filtration rate, filtration fraction, creatinine clearance, or renal plasma flow.

In multiple-dose studies in hypertensive patients, valsartan had no notable effects on total cholesterol, fasting triglycerides, fasting serum glucose, or uric acid.

Hydrochlorothiazide: After oral administration of hydrochlorothiazide, diuresis begins within 2 hours, peaks in about 4 hours and lasts about 6 to 12 hours.

12.3 Pharmacokinetics

Valsartan: Valsartan peak plasma concentration is reached 2 to 4 hours after dosing. Valsartan shows bi-exponential decay kinetics following intravenous administration, with an average elimination half-life of about 6 hours. Absolute bioavailability for the capsule formulation is about 25% (range 10%-35%). Food decreases the exposure (as measured by AUC) to valsartan by about 40% and peak plasma concentration (Cmax) by about 50%. AUC and Cmax values of valsartan increase approximately linearly with increasing dose over the clinical dosing range. Valsartan does not accumulate appreciably in plasma following repeated administration.

Hydrochlorothiazide: Thiazide diuretics are eliminated by the kidney, with a terminal half-life of 5-15 hours.

Geriatric: Exposure (measured by AUC) to valsartan is higher by 70% and the half-life is longer by 35% in the elderly than in the young. No dosage adjustment is necessary [See Dosage and Administration (2.1)].

Gender: Pharmacokinetics of valsartan does not differ significantly between males and females.

Race: Pharmacokinetic differences due to race have not been studied.

Renal Insufficiency: There is no apparent correlation between renal function (measured by creatinine clearance) and exposure (measured by AUC) to valsartan in patients with different degrees of renal impairment. Consequently, dose adjustment is not required in patients with mild-to-moderate renal dysfunction. No studies have been performed in patients with severe impairment of renal function (creatinine clearance greater than 10 mL/min). Valsartan is not removed from the plasma by hemodialysis. In the case of severe renal disease, exercise care with dosing of valsartan [See Dosage and Administration (2.1)].

In a study of patients with impaired renal function (mean creatinine clearance of 19 mL/min), the half-life of hydrochlorothiazide elimination was lengthened to 21 hours.

Hepatic Insufficiency: On average, patients with mild-to-moderate chronic liver disease have twice the exposure (measured by AUC values) to valsartan of healthy volunteers (matched by age, sex, and weight). In general, no dosage adjustment is needed in patients with mild-to-moderate liver disease. Care should be exercised in patients with liver disease [See Dosage and Administration (2.1)].

Distribution

Valsartan: The steady state volume of distribution of valsartan after intravenous administration is small (17 L), indicating that valsartan does not distribute into tissues extensively. Valsartan is highly bound to serum proteins (95%), mainly serum albumin.

Hydrochlorothiazide: Hydrochlorothiazide crosses the placental but not the blood-brain barrier and is excreted in breast milk.

Metabolism

Valsartan: The primary metabolite, accounting for about 9% of dose, is valeryl 4-hydroxy valsartan. The enzyme(s) responsible for valsartan metabolism have not been identified but do not seem to be CYP 450 isozymes.

Hydrochlorothiazide: Is not metabolized.

Excretion

Valsartan: Valsartan, when administered as an oral solution, is primarily recovered in feces (about 83% of dose) and urine (about 13% of dose). The recovery is mainly as unchanged drug, with only about 20% of dose recovered as metabolites.

Following intravenous administration, plasma clearance of valsartan is about 2 L/h and its renal clearance is 0.62 L/h (about 30% of total clearance).

Hydrochlorothiazide: Hydrochlorothiazide is not metabolized but is eliminated rapidly by the kidney. At least 61% of the oral dose is eliminated as unchanged drug within 24 hours. The elimination half-life is between 5.8 and 18.9 hours

2 DOSAGE AND ADMINISTRATION 2.1 General Considerations

The side effects of valsartan are generally rare and appear independent of dose. Those of hydrochlorothiazide are a mixture of dose-dependent (primarily hypokalemia) and dose-independent phenomena (e.g., pancreatitis), the former much more common than the latter [See Adverse Reactions (6)].

Dose once-daily. Maximum antihypertensive effects are attained within 2 to 4 weeks after a change in dose.

Diovan HCT may be administered with or without food.

Diovan HCT may be administered with other antihypertensive agents.

Elderly patients: No initial dosage adjustment is required for elderly patients.

Renal impairment: The usual regimens of therapy with Diovan HCT may be followed as long as the patient’s creatinine clearance is >30 mL/min. In patients with more severe renal impairment, loop diuretics are preferred to thiazides, so Diovan HCT is not recommended.

Hepatic impairment: Care should be exercised with dosing of Diovan HCT in patients with hepatic impairment. Start with a low dose and titrate slowly in patients with hepatic impairment [See Impaired Hepatic Function (5.3)].

2.2 Add-On Therapy

A patient whose blood pressure is not adequately controlled with valsartan (or another ARB) alone or hydrochlorothiazide alone may be switched to combination therapy with Diovan HCT.

A patient who experiences dose-limiting adverse reactions on either component alone may be switched to Diovan HCT containing a lower dose of that component in combination with the other to achieve similar blood pressure reductions. The clinical response to Diovan HCT should be subsequently evaluated and if blood pressure remains uncontrolled after 3 to 4 weeks of therapy, the dose may be titrated up to a maximum of 320/25 mg.

2.3 Replacement Therapy

Diovan HCT may be substituted for the titrated components.

2.4 Initial Therapy
The usual starting dose is Diovan HCT 160/12.5 mg once daily. The dosage can be increased after 1 to 2 weeks of therapy to a maximum of one 320/25 mg tablet once daily as needed to control blood pressure [See Clinical Studies (14.2)]. Diovan HCT is not recommended as initial therapy in patients with intravascular volume depletion [See Warnings and Precautions (5.2)].

16 HOW SUPPLIED/STORAGE AND HANDLING

Diovan HCT (valsartan and hydrochlorothiazide, USP) is available as non-scored tablets containing valsartan/hydrochlorothiazide 80/12.5 mg, 160/12.5 mg, 160/25 mg, 320/12.5 mg and 320/25 mg. strengths are available as follows.

80/12.5 mg Tablet - Light orange, ovaloid with slightly convex faces debossed CG on one side and HGH on the other side.

Bottles of 90 NDC 0078-0314-34

Unit Dose (blister pack) NDC 0078-0314-06

Box of 100 (strips of 10)

160/12.5 mg Tablet - Dark red, ovaloid with slightly convex faces debossed CG on one side and HHH on the other side.

Bottles of 90 NDC 0078-0315-34

Unit Dose (blister pack) NDC 0078-0315-06

Box of 100 (strips of 10)

Unit Dose (blister Pack of 30) NDC 0078-0315-15

160/25 mg Tablet - Brown orange, ovaloid with slightly convex faces debossed NVR on one side and HXH on the other side.

Bottles of 90 NDC 0078-0383-34

Unit Dose (blister pack) NDC 0078-0383-06

Box of 100 (strips of 10)

Unit Dose (blister pack of 30) NDC 0078-0383-15

320/12.5 mg Tablet - Pink, ovaloid with beveled edge, debossed NVR on one side and HIL on the other side.

Bottles of 90 NDC 0078-0471-34

Unit Dose (blister pack) NDC 0078-0471-06

Box of 100 (strips of 10)

Unit Dose (blister pack of 30) NDC 0078-0471-15

320/25 mg Tablet - Yellow, ovaloid with beveled edge, debossed NVR on one side and CTI on the other side.

Bottles of 90 NDC 0078-0472-34

Unit Dose (blister pack) NDC 0078-0472-06

Box of 100 (strips of 10)

Unit Dose (blister pack of 30) NDC 0078-0472-15

Store at 25ºC (77ºF); excursions permitted to 15-30ºC (59-86ºF) [see USP Controlled Room Temperature].

Protect from moisture.

Dispense in tight container (USP).

PATIENT COUNSELING INFORMATION 17.1 Information for Patients

Pregnancy: Female patients of childbearing age should be told that use of drugs like Diovan HCT that act on the renin-angiotensin system during pregnancy can cause serious problems in the fetus and infant including: low blood pressure, poor development of skull bones, kidney failure and death. Discuss other treatment options with female patients planning to become pregnant. Women using Diovan HCT who become pregnant should notify their physician as soon as possible.

Symptomatic Hypotension: A patient receiving Diovan HCT should be cautioned that lightheadedness can occur, especially during the first days of therapy, and that it should be reported to the prescribing physician. The patients should be told that if syncope occurs, Diovan HCT should be discontinued until the physician has been consulted.

All patients should be cautioned that inadequate fluid intake, excessive perspiration, diarrhea, or vomiting can lead to an excessive fall in blood pressure, with the same consequences of lightheadedness and possible syncope.

Potassium Supplements: A patient receiving Diovan HCT should be told not to use potassium supplements or salt substitutes containing potassium without consulting the prescribing physician.

WARNING: AVOID USE IN PREGNANCY

When pregnancy is detected, discontinue Diovan HCT® as soon as possible. Drugs that act directly on the renin-angiotensin system can cause injury and even death to the developing fetus. [See Warnings and Precautions (5.1)]

PATIENT INFORMATION

DIOVAN HCT (DYE’-o-van HCT)

(valsartan and hydrochlorothiazide)

Tablets

Read the Patient Information that comes with DIOVAN HCT before you start taking it and each time you get a refill. There may be new information. This leaflet does not take the place of talking with your doctor about your condition and treatment. If you have any questions about DIOVAN HCT, ask your doctor or pharmacist.

What is the most important information I should know about DIOVAN HCT?
If you become pregnant, stop taking DIOVAN HCT and call your doctor right away. DIOVAN HCT can harm an unborn baby causing injury and even death. If you plan to become pregnant, talk to your doctor about other treatment options to lower your high blood pressure before taking DIOVAN HCT.

What is DIOVAN HCT?

DIOVAN HCT contains two prescription medicines:

1. valsartan, an angiotensin receptor blocker (ARB)
2. hydrochlorothiazide (HCTZ), a water pill (diuretic)

DIOVAN HCT may be used to lower high blood pressure (hypertension) in adults-

- when one medicine to lower your high blood pressure is not enough
- as the first medicine to lower high blood pressure if your doctor decides you are likely to need more than one medicine.

DIOVAN HCT has not been studied in children under 18 years of age.

Who should not take DIOVAN HCT?

Do not take DIOVAN HCT if you:

- are allergic to any of the ingredients in DIOVAN HCT. See the end of this leaflet for a complete list of ingredients in DIOVAN HCT.
- make less urine due to kidney problems
- are allergic to medicines that contain sulfonamides.

What should I tell my doctor before taking DIOVAN HCT?

Tell your doctor about all your medical conditions including if you:

- are pregnant or plan to become pregnant. See “What is the most important information I should know about DIOVAN HCT?”
- are breast-feeding. DIOVAN HCT passes into breast milk. You should choose either to take DIOVAN HCT or breast-feed, but not both.
- have liver problems
- have kidney problems
- have or had gallstones
- have Lupus

Tell your doctor about all the medicines you take including prescription and nonprescription medicines, vitamins and herbal supplements. Some of your other medicines and DIOVAN HCT could affect each other, causing serious side effects. Especially, tell your doctor if you take:

- other medicines for high blood pressure or a heart problem
- water pills (diuretics)
- potassium supplements
- a salt substitute containing potassium
- antidiabetic medicines including insulin
- narcotic pain medicines
- sleeping pills
- lithium, a medicine used in some types of depression (Eskalith®, Lithobid®, Lithium Carbonate, Lithium Citrate)
- aspirin or other medicines called Non-Steroidal Anti-Inflammatory Drugs (NSAIDs).

Ask your doctor if you are not sure if you are taking one of these medicines.

Know the medicines you take. Keep a list of your medicines with you to show to your doctor and pharmacist when a new medicine is prescribed. Talk to your doctor or pharmacist before you start taking any new medicine. Your doctor or pharmacist will know what medicines are safe to take together.

How should I take DIOVAN HCT?

- Take DIOVAN HCT exactly as prescribed by your doctor. Your doctor may change your dose if needed.
- Take DIOVAN HCT once each day.
- DIOVAN HCT can be taken with or without food.
- If you miss a dose, take it as soon as you remember. If it is close to your next dose, do not take the missed dose. Just take the next dose at your regular time.
- If you take too much DIOVAN HCT, call your doctor or Poison Control Center, or go to the nearest hospital emergency room.

What should I avoid while taking DIOVAN HCT?

You should not take DIOVAN HCT during pregnancy. See “What is the most important information I should know about DIOVAN HCT?”

What are the possible side effects of DIOVAN HCT?

DIOVAN HCT may cause serious side effects including:

- Harm to an unborn baby causing injury and even death. See “What is the most important information I should know about DIOVAN HCT?”
- Low blood pressure (hypotension). Low blood pressure is most likely to happen if you:
  - take water pills
  - are on a low salt diet
  - get dialysis treatments
  - have heart problems
  - get sick with vomiting or diarrhea
  - drink alcohol

Lie down if you feel faint or dizzy. Call your doctor right away.

- Worsening liver problems. Liver problems may get worse in people who already have liver problems and take DIOVAN HCT.
- Allergic reactions. People with and without allergy problems or asthma who take DIOVAN HCT may get allergic reactions.
- Worsening of Lupus. Hydrochlorothiazide, one of the medicines in DIOVAN HCT may cause Lupus to become active or worse.
- Fluid and electrolyte (salt) problems. Tell your doctor about any of the following signs and symptoms of fluid and electrolyte problems:

- dry mouth
- thirst
- lack of energy (lethargic)
- weakness

- drowsiness
- restlessness
- confusion
- seizures
- muscle pain or cramps

- muscle fatigue
- very low urine output
- fast heartbeat
- nausea and vomiting

- Kidney problems. Kidney problems may become worse in people that already have kidney disease. Some people will have changes on blood tests for kidney function and may need a lower dose of DIOVAN HCT. Call your doctor if you get swelling in your feet, ankles, or hands, or unexplained weight gain. If you have heart failure, your doctor should check your kidney function before prescribing DIOVAN HCT.
- Skin rash. Call your doctor right away if you have an unusual skin rash.

Other side effects were generally mild and brief. They generally have not caused patients to stop taking DIOVAN HCT.

Tell your doctor if you have any side effect that bothers you or that does not go away.

These are not all the possible side effects of DIOVAN HCT. For a complete list, ask your doctor or pharmacist.

Call your doctor for medical advice about side effects. You may report side effects to FDA at 1-800-FDA-1088.

How do I store DIOVAN HCT?

- Store DIOVAN HCT tablets at room temperature between 59oF to 86oF (15oC to 30oC).
- Keep DIOVAN HCT in a closed container in a dry place.

Keep DIOVAN HCT and all medicines out of the reach of children.

General information about DIOVAN HCT

Medicines are sometimes prescribed for conditions that are not mentioned in patient information leaflets. Do not use DIOVAN HCT for a condition for which it was not prescribed. Do not give DIOVAN HCT to other people, even if they have the same symptoms you have. It may harm them.

This leaflet summarizes the most important information about DIOVAN HCT. If you would like more information, talk with your doctor. You can ask your doctor or pharmacist for information about DIOVAN HCT that is written for health professionals. For more information about DIOVAN HCT, go to www.DIOVAN.com or call 1-866-404-6359.

What are the ingredients in DIOVAN HCT?

Active ingredients: Valsartan and hydrochlorothiazide

Inactive ingredients: colloidal silicon dioxide, crospovidone, hydroxypropyl methylcellulose, iron oxides, magnesium stearate, microcrystalline cellulose, polyethylene glycol, talc, and titanium dioxide.

What is high blood pressure (hypertension)?

Blood pressure is the force in your blood vessels when your heart beats and when your heart rests. You have high blood pressure when the force is too much. DIOVAN HCT can help your blood vessels relax and reduce the amount of water in your body so your blood pressure is lower. Medicines that lower blood pressure lower your risk of having a stroke or heart attack.

High blood pressure makes the heart work harder to pump blood throughout the body and causes damage to the blood vessels. If high blood pressure is not treated, it can lead to stroke, heart attack, heart failure, kidney failure, and vision problems.

Eskalith® and Lithobid® are registered trademarks of Noven Pharmaceuticals, Inc.

Distributed by:

Novartis Pharmaceuticals Corporation

East Hanover, New Jersey 07936

© Novartis

Revised: MAY 2009 T2009-54/T2008-20

DIOVAN LABEL